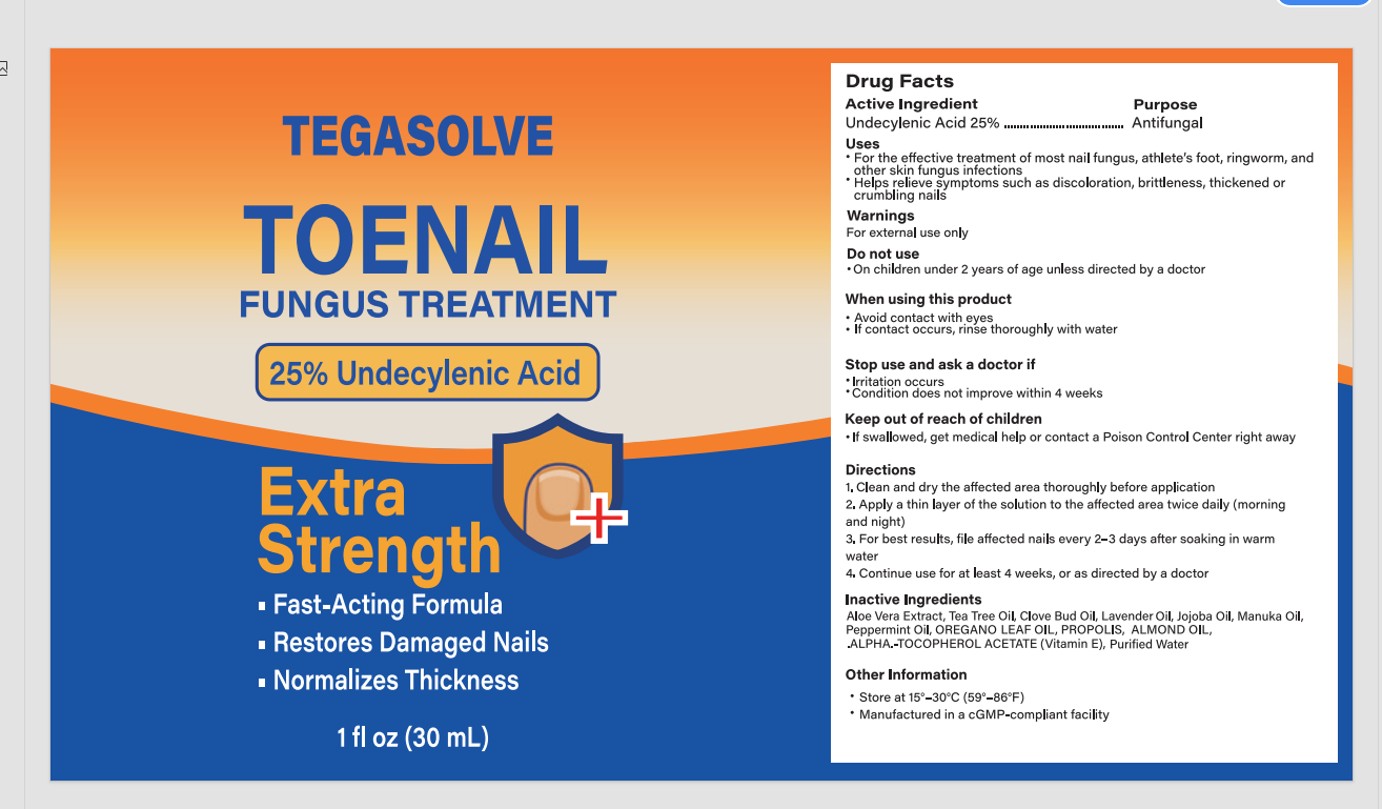 DRUG LABEL: TEGASOLVE TOENAIL FUNGUS TREATMENT
NDC: 85578-003 | Form: LIQUID
Manufacturer: Zhengzhou Hangrui Network Technology Co., Ltd.
Category: otc | Type: HUMAN OTC DRUG LABEL
Date: 20250612

ACTIVE INGREDIENTS: UNDECYLENIC ACID 25 g/100 mL
INACTIVE INGREDIENTS: JOJOBA OIL; ALMOND OIL; PROPOLIS WAX; .ALPHA.-TOCOPHEROL ACETATE; WATER; MANUKA OIL; LAVENDER OIL; CLOVE OIL; OREGANO LEAF OIL; PEPPERMINT OIL; ALOE VERA LEAF; TEA TREE OIL

85578-003 TEGASOLVE TOENAIL FUNGUS TREATMENT

ACTIVE INGREDIENT

Undecylenic Acid 25%

PURPOSE

Antifungal

INDICATIONS AND USAGE

For the effective treatment of most nail fungus, athlete's foot, ringworm, andother skin fungus infections
Helps relieve symptoms such as discoloration, brittleness, thickened orcrumbling nails

WARNINGS

For external use only

DO NOT USE

On children under 2 years of age unless directed by a doctor

WHEN USING

Avoid contact with eyes
If contact occurs, rinse thoroughly with water

STOP USE

Irritation occurs
Condition does not improve within 4 weeks

KEEP OUT OF REACH OF CHILDREN

lf swallowed, get medical help or contact a Poison Control Center right away

DOSAGE AND ADMINISTRATION

1, Clean and dry the affected area thoroughly before application
2, Apply a thin layer of the solution to the affected area twice daily(morningand night)
3, For best results, file affected nails every 2-3 days after soaking in warmwater
4, Continue use for at least 4 weeks, or as directed by a doctor

INACTIVE INGREDIENT

Aloe Vera Extract
Tea Tree Oil
Clove Bud Oil
Lavender Oil
Jojoba Oil
Manuka Oil
Peppermint Oil
OREGANO LEAF OIL
PROPOLIS
ALMOND OIL
.ALPHA.-TOCOPHEROL ACETATE (Vitamin E)
Purified Water